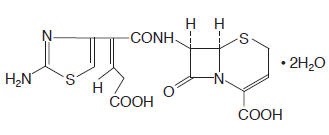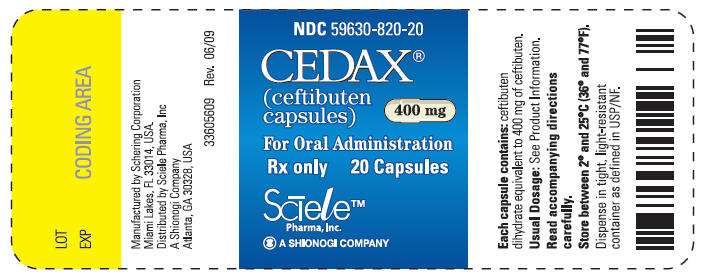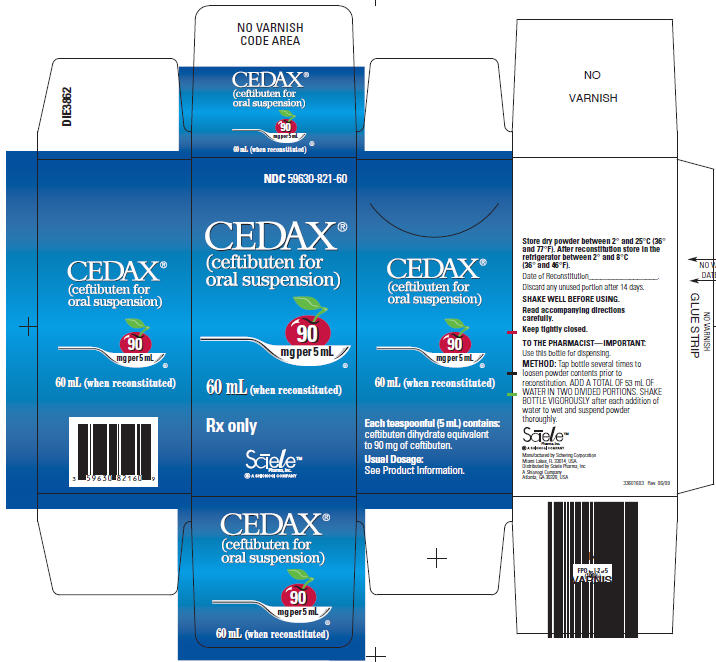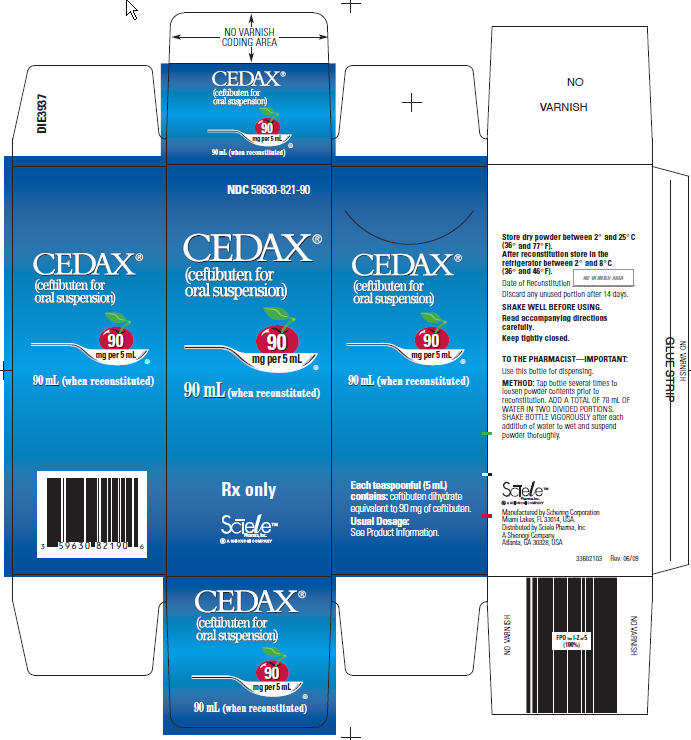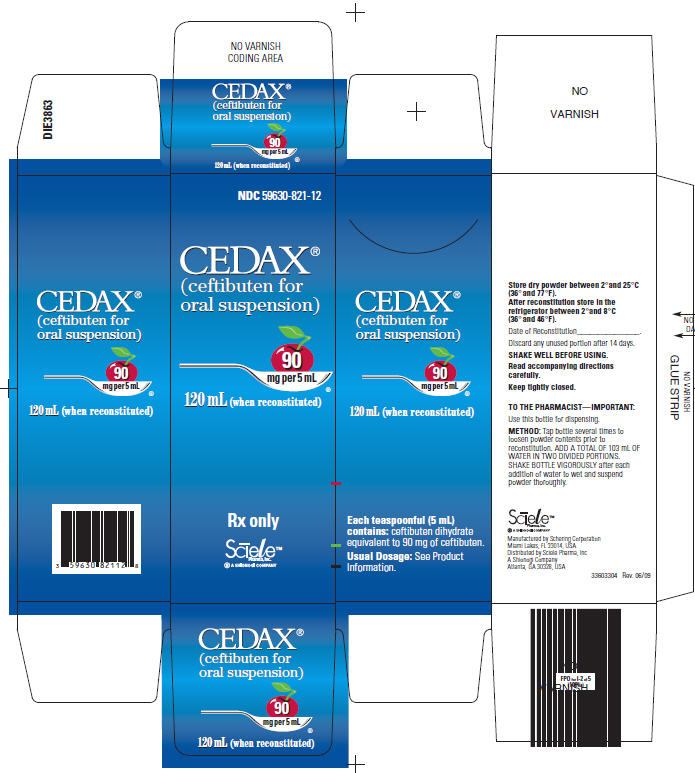 DRUG LABEL: Cedax
NDC: 59630-820 | Form: CAPSULE
Manufacturer: Sciele Pharma, Inc.
Category: prescription | Type: HUMAN PRESCRIPTION DRUG LABEL
Date: 20100112

ACTIVE INGREDIENTS: Ceftibuten dihydrate 400 mg/1 1
INACTIVE INGREDIENTS: gelatin; sodium lauryl sulfate; titanium dioxide; polysorbate 80; benzyl alcohol; sodium propionate; edetate calcium disodium; butylparaben; propylparaben; methylparaben

CEDAX®
(ceftibuten capsules)
and
(ceftibuten for oral suspension)

FOR ORAL USE ONLY

PRODUCT INFORMATION

DESCRIPTION

CEDAX (ceftibuten capsules) and (ceftibuten for oral suspension) contain the active ingredient ceftibuten as ceftibuten dihydrate. Ceftibuten dihydrate is a semisynthetic cephalosporin antibiotic for oral administration. Chemically, it is (+)-(6R,7R)-7-[(Z)-2-(2-Amino-4-thiazolyl)-4-carboxycrotonamido]-8-oxo-5-thia-1-azabicyclo[4.2.0]oct-2-ene-2-carboxylic acid, dihydrate. Its molecular formula is C15H14N4O6S2•2H2O. Its molecular weight is 446.43 as the dihydrate.

Ceftibuten dihydrate has the following structural formula:

CEDAX Capsules contain ceftibuten dihydrate equivalent to 400 mg of ceftibuten. Inactive ingredients contained in the capsule formulation include: magnesium stearate, microcrystalline cellulose, and sodium starch glycolate. The capsule shell and/or band contains gelatin, sodium lauryl sulfate, titanium dioxide, and polysorbate 80. The capsule shell may also contain benzyl alcohol, sodium propionate, edetate calcium disodium, butylparaben, propylparaben, and methylparaben.

CEDAX Oral Suspension after reconstitution contains ceftibuten dihydrate equivalent to 90 mg of ceftibuten per 5 mL. CEDAX Oral Suspension is cherry flavored and contains the inactive ingredients: cherry flavoring, polysorbate 80, silicon dioxide, simethicone, sodium benzoate, sucrose (approximately 1 g/5 mL), titanium dioxide, and xanthan gum.

CLINICAL PHARMACOLOGY

PHARMACOKINETICS

Absorption

CEDAX CAPSULES

Ceftibuten is rapidly absorbed after oral administration of CEDAX Capsules. The plasma concentrations and pharmacokinetic parameters of ceftibuten after a single 400-mg dose of CEDAX Capsules to 12 healthy adult male volunteers (20 to 39 years of age) are displayed in the table below. When CEDAX Capsules were administered once daily for 7 days, the average Cmax was 17.9 µg/mL on day 7. Therefore, ceftibuten accumulation in plasma is about 20% at steady state.

CEDAX ORAL SUSPENSION

Ceftibuten is rapidly absorbed after oral administration of CEDAX Oral Suspension. The plasma concentrations and pharmacokinetic parameters of ceftibuten after a single 9-mg/kg dose of CEDAX Oral Suspension to 32 fasting pediatric patients (6 months to 12 years of age) are displayed in the following table:

Parameter | Average Plasma Concentration (in µg/mL of ceftibuten after a single 400-mg dose) and Derived Pharmacokinetic Parameters (± 1 SD) (n = 12 healthy adult males) | Average Plasma Concentration (in µg/mL of ceftibuten after a single 9-mg/kg dose) and Derived Pharmacokinetic Parameters (± 1 SD) (n = 32 pediatric patients)
1.0 h | 6.1 (5.1) | 9.3 (6.3)
1.5 h | 9.9 (5.9) | 8.6 (4.4)
2.0 h | 11.3 (5.2) | 11.2 (4.6)
3.0 h | 13.3 (3.0) | 9.0 (3.4)
4.0 h | 11.2 (2.9) | 6.6 (3.1)
6.0 h | 5.8 (1.6) | 3.8 (2.5)
8.0 h | 3.2 (1.0) | 1.6 (1.3)
12.0 h | 1.1 (0.4) | 0.5 (0.4)
Cmax, µg/mL | 15.0 (3.3) | 13.4 (4.9)
Tmax, h | 2.6 (0.9) | 2.0 (1.0)
AUC, µg∙h/mL | 73.7 (16.0) | 56.0 (16.9)
T½, h | 2.4 (0.2) | 2.0 (0.6)
Total body clearance (CI/F) mL/min/kg | 1.3 (0.3) | 2.9 (0.7)

The absolute bioavailability of CEDAX Oral Suspension has not been determined. The plasma concentrations of ceftibuten in pediatric patients are dose proportional following single doses of CEDAX Capsules of 200 mg and 400 mg and of CEDAX Oral Suspension between 4.5 mg/kg and 9 mg/kg.

Distribution

CEDAX CAPSULES

The average apparent volume of distribution (V/F) of ceftibuten in 6 adult subjects is 0.21 L/kg (± 1 SD = 0.03 L/kg).

CEDAX ORAL SUSPENSION

The average apparent volume of distribution (V/F) of ceftibuten in 32 fasting pediatric patients is 0.5 L/kg (± 1 SD = 0.2 L/kg).

Protein Binding

Ceftibuten is 65% bound to plasma proteins. The protein binding is independent of plasma ceftibuten concentration.

Tissue Penetration

Bronchial secretions

In a study of 15 adults administered a single 400-mg dose of ceftibuten and scheduled to undergo bronchoscopy, the mean concentrations in epithelial lining fluid and bronchial mucosa were 15% and 37%, respectively, of the plasma concentrations.

Sputum

Ceftibuten sputum levels average approximately 7% of the concomitant plasma ceftibuten level. In a study of 24 adults administered ceftibuten 200 mg bid or 400 mg qd, the average Cmax in sputum (1.5 µg/mL) occurred at 2 hours postdose and the average Cmax in plasma (17 µg/mL) occurred at 2 hours postdose.

Middle-ear fluid (MEF)

In a study of 12 pediatric patients administered 9 mg/kg, ceftibuten MEF area under the curve (AUC) averaged approximately 70% of the plasma AUC. In the same study, Cmax values were 14.3 ± 2.7 µg/mL in MEF at 4 hours postdose and 14.5 ± 3.7 µg/mL in plasma at 2 hours postdose.

Tonsillar tissue

Data on ceftibuten penetration into tonsillar tissue are not available.

Cerebrospinal fluid

Data on ceftibuten penetration into cerebrospinal fluid are not available.

Metabolism and Excretion

A study with radiolabeled ceftibuten administered to 6 healthy adult male volunteers demonstrated that cis-ceftibuten is the predominant component in both plasma and urine. About 10% of ceftibuten is converted to the trans-isomer. The trans-isomer is approximately ⅛ as antimicrobially potent as the cis-isomer.

Ceftibuten is excreted in the urine; 95% of the administered radioactivity was recovered either in urine or feces. In 6 healthy adult male volunteers, approximately 56% of the administered dose of ceftibuten was recovered from urine and 39% from the feces within 24 hours. Because renal excretion is a significant pathway of elimination, patients with renal dysfunction and patients undergoing hemodialysis require dosage adjustment (see DOSAGE AND ADMINISTRATION).

Food Effect on Absorption

Food affects the bioavailability of ceftibuten from CEDAX Capsules and CEDAX Oral Suspension.

The effect of food on the bioavailability of CEDAX Capsules was evaluated in 26 healthy adult male volunteers who ingested 400 mg of CEDAX Capsules after an overnight fast or immediately after a standardized breakfast. Results showed that food delays the time of Cmax by 1.75 hours, decreases the Cmax by 18%, and decreases the extent of absorption (AUC) by 8%.

The effect of food on the bioavailability of CEDAX Oral Suspension was evaluated in 18 healthy adult male volunteers who ingested 400 mg of CEDAX Oral Suspension after an overnight fast or immediately after a standardized breakfast. Results obtained demonstrated a decrease in Cmax of 26% and an AUC of 17% when CEDAX Oral Suspension was administered with a high-fat breakfast, and a decrease in Cmax of 17% and an AUC of 12% when CEDAX Oral Suspension was administered with a low-calorie nonfat breakfast (see PRECAUTIONS).

Bioequivalence of Dosage Formulations

A study in 18 healthy adult male volunteers demonstrated that a 400-mg dose of CEDAX Capsules produced equivalent concentrations to a 400-mg dose of CEDAX Oral Suspension. Average Cmax values were 15.6 (3.1) µg/mL for the capsule and 17.0 (3.2) µg/mL for the suspension. Average AUC values were 80.1 (14.4) µg∙hr/mL for the capsule and 87.0 (12.2) µg∙hr/mL for the suspension.

Special Populations

Geriatric patients

Ceftibuten pharmacokinetics have been investigated in elderly (65 years of age and older) men (n = 8) and women (n = 4). Each volunteer received ceftibuten 200-mg capsules twice daily for 3½ days. The average Cmax was 17.5 (3.7) µg/mL after 3½ days of dosing compared to 12.9 (2.1) µg/mL after the first dose; ceftibuten accumulation in plasma was 40% at steady state. Information regarding the renal function of these volunteers was not available; therefore, the significance of this finding for clinical use of CEDAX Capsules in elderly patients is not clear. Ceftibuten dosage adjustment in elderly patients may be necessary (see DOSAGE AND ADMINISTRATION).

Patients with renal insufficiency

Ceftibuten pharmacokinetics have been investigated in adult patients with renal dysfunction. The ceftibuten plasma half-life increased and apparent total clearance (CI/F) decreased proportionately with increasing degree of renal dysfunction. In 6 patients with moderate renal dysfunction (creatinine clearance 30 to 49 mL/min), the plasma half-life of ceftibuten increased to 7.1 hours and CI/F decreased to 30 mL/min. In 6 patients with severe renal dysfunction (creatinine clearance 5 to 29 mL/min), the half-life increased to 13.4 hours and CI/F decreased to 16 mL/min. In 6 functionally anephric patients (creatinine clearance <5 mL/min), the half-life increased to 22.3 hours and CI/F decreased to 11 mL/min (a 7- to 8-fold change compared to healthy volunteers). Hemodialysis removed 65% of the drug from the blood in 2 to 4 hours. These changes serve as the basis for dosage adjustment recommendations in adult patients with mild to severe renal dysfunction (see DOSAGE AND ADMINISTRATION).

Microbiology

Ceftibuten exerts its bactericidal action by binding to essential target proteins of the bacterial cell wall. This binding leads to inhibition of cell-wall synthesis.

Ceftibuten is stable in the presence of most plasmid-mediated beta-lactamases, but it is not stable in the presence of chromosomally-mediated cephalosporinases produced in organisms such as Bacteroides, Citrobacter, Enterobacter, Morganella, and Serratia. Like other beta-lactam agents, ceftibuten should not be used against strains resistant to beta-lactams due to general mechanisms such as permeability or penicillin-binding protein changes like penicillin-resistant S. pneumoniae.

Ceftibuten has been shown to be active against most strains of the following organisms both in vitro and in clinical infections (see INDICATIONS AND USAGE):

Gram-positive aerobes:

Streptococcus pneumoniae (penicillin-susceptible strains only)
Streptococcus pyogenes

Gram-negative aerobes:

Haemophilus influenzae (including β-lactamase-producing strains)
Moraxella catarrhalis (including β-lactamase-producing strains)

There are no known organisms which are potential pathogens in the indications approved for ceftibuten for which ceftibuten exhibits in vitro activity but for which the safety and efficacy of ceftibuten in treating clinical infections due to these organisms, have not been established in adequate and well-controlled trials.

NOTE: Ceftibuten is INACTIVE in vitro against Acinetobacter, Bordetella, Campylobacter, Enterobacter, Enterococcus, Flavobacterium, Hafnia, Listeria, Pseudomonas, Staphylococcus, and Streptococcus (except pneumoniae and pyogenes) species. In addition, it shows little in vitro activity against most anaerobes, including most species of Bacteroides.

Susceptibility Testing

Dilution Techniques

Quantitative methods are used to determine antimicrobial minimal inhibitory concentrations (MICs). These MICs provide estimates of the susceptibility of bacteria to antimicrobial compounds. The MICs should be determined using a standardized procedure. Standardized procedures are based on a dilution method (broth, agar, or microdilution) or equivalent with standardized inoculum concentrations and standardized concentrations of ceftibuten powder. The MIC values should be interpreted according to the following criteria when testing Haemophilus species using Haemophilus Test Media (HTM):

MIC (µg/mL) | Interpretation
≤2 | (S) Susceptible

The current absence of resistant strains precludes defining any categories other than "Susceptible". Strains yielding results suggestive of a "Nonsusceptible" category should be submitted to a reference laboratory for further testing.

A report of "Susceptible" implies that an infection due to the strain may be appropriately treated with the dosage of antimicrobial agent recommended for that type of infection and infecting species, unless otherwise contraindicated.

Ceftibuten is indicated for penicillin-susceptible only strains of Streptococcus pneumoniae. A pneumococcal isolate that is susceptible to penicillin (MIC ≤0.06 µg/mL) can be considered susceptible to ceftibuten for approved indications. Testing of ceftibuten against penicillin-intermediate or penicillin resistant isolates is not recommended. Reliable interpretive criteria for ceftibuten are not currently available. Physicians should be informed that clinical response rates with ceftibuten may be lower in strains that are not penicillin-susceptible.

Standardized susceptibility test procedures require the use of laboratory control microorganisms to control the technical aspect of laboratory procedures. Standard ceftibuten powder should provide the following MIC values:

Organism | MIC range (µg/mL)
Haemophilus influenzae ATCC 49247 | 0.25-1.0

Diffusion Techniques

Quantitative methods that require measurement of zone diameters also provide estimates of the susceptibility of bacteria to antimicrobial compounds. One such standardized procedure requires the use of standardized inoculum concentrations. This procedure uses paper disks impregnated with 30 µg of ceftibuten to test the susceptibility of microorganisms to ceftibuten.

Reports from the laboratory providing results of the standard single-disk susceptibility test with a 30-µg ceftibuten disk should be interpreted according to the following criteria when testing Haemophilus species using Haemophilus Test Media (HTM):

Zone diameter (mm) | Interpretation
≥28 | (S) Susceptible

The current absence of resistant strains precludes defining any categories other than "Susceptible". Strains yielding results suggestive of a "Nonsusceptible" category should be submitted to a reference laboratory for further testing.

Interpretation should be as stated above for results using dilution techniques.

Ceftibuten is indicated for penicillin-susceptible only strains of Streptococcus pneumoniae. Pneumococcal isolates with oxacillin zone sizes of ≥20 mm are susceptible to penicillin and can be considered susceptible for approved indications. Reliable disk diffusion tests for ceftibuten do not yet exist.

As with standardized dilution techniques, diffusion methods require the use of laboratory control microorganisms that are used to control the technical aspects of the laboratory procedures. For the diffusion technique, the 30-µg ceftibuten disk should provide the following zone diameters in these laboratory test quality control strains:

Organism | Zone diameter (mm)
Haemophilus influenzae ATCC 49247 | 29-35

Cephalosporin-class disks should not be used to test for susceptibility to ceftibuten.

INDICATIONS AND USAGE

CEDAX (ceftibuten) is indicated for the treatment of individuals with mild-to-moderate infections caused by susceptible strains of the designated microorganisms in the specific conditions listed below (see DOSAGE AND ADMINISTRATION and CLINICAL STUDIES sections).

Acute Bacterial Exacerbations of Chronic Bronchitis due to Haemophilus influenzae (including β-lactamase-producing strains), Moraxella catarrhalis (including β-lactamase-producing strains), or Streptococcus pneumoniae (penicillin-susceptible strains only).

NOTE: In acute bacterial exacerbations of chronic bronchitis clinical trials where Moraxella catarrhalis was isolated from infected sputum at baseline, ceftibuten clinical efficacy was 22% less than control.

Acute Bacterial Otitis Media due to Haemophilus influenzae (including β-lactamase-producing strains), Moraxella catarrhalis (including β-lactamase-producing strains), or Streptococcus pyogenes.

NOTE: Although ceftibuten used empirically was equivalent to comparators in the treatment of clinically and/or microbiologically documented acute otitis media, the efficacy against Streptococcus pneumoniae was 23% less than control. Therefore, ceftibuten should be given empirically only when adequate antimicrobial coverage against Streptococcus pneumoniae has been previously administered.

Pharyngitis and Tonsillitis due to Streptococcus pyogenes.

NOTE: Only penicillin by the intramuscular route of administration has been shown to be effective in the prophylaxis of rheumatic fever. Ceftibuten is generally effective in the eradication of Streptococcus pyogenes from the oropharynx; however, data establishing the efficacy of the CEDAX product for the prophylaxis of subsequent rheumatic fever are not available.

CONTRAINDICATIONS

CEDAX (ceftibuten) is contraindicated in patients with known allergy to the cephalosporin group of antibiotics.

WARNINGS

BEFORE THERAPY WITH THE CEDAX PRODUCT IS INSTITUTED, CAREFUL INQUIRY SHOULD BE MADE TO DETERMINE WHETHER THE PATIENT HAS HAD PREVIOUS HYPERSENSITIVITY REACTIONS TO CEFTIBUTEN, OTHER CEPHALOSPORINS, PENICILLINS, OR OTHER DRUGS. IF THIS PRODUCT IS TO BE GIVEN TO PENICILLIN-SENSITIVE PATIENTS, CAUTION SHOULD BE EXERCISED BECAUSE CROSS HYPERSENSITIVITY AMONG BETA-LACTAM ANTIBIOTICS HAS BEEN CLEARLY DOCUMENTED AND MAY OCCUR IN UP TO 10% OF PATIENTS WITH A HISTORY OF PENICILLIN ALLERGY. IF AN ALLERGIC REACTION TO THE CEDAX PRODUCT OCCURS, DISCONTINUE THE DRUG. SERIOUS ACUTE HYPERSENSITIVITY REACTIONS MAY REQUIRE TREATMENT WITH EPINEPHRINE AND OTHER EMERGENCY MEASURES, INCLUDING OXYGEN, INTRAVENOUS FLUIDS, INTRAVENOUS ANTIHISTAMINES, CORTICOSTEROIDS, PRESSOR AMINES, AND AIRWAY MANAGEMENT, AS CLINICALLY INDICATED.

Pseudomembranous colitis has been reported with nearly all antibacterial agents, including ceftibuten, and may range in severity from mild to life threatening. Therefore, it is important to consider this diagnosis in patients who present with diarrhea subsequent to the administration of antibacterial agents.

Treatment with antibacterial agents alters normal flora of the colon and may permit overgrowth of clostridia. Studies indicate that a toxin produced by Clostridium difficile is one primary cause of "antibiotic-associated colitis".

After the diagnosis of pseudomembranous colitis has been established, appropriate therapeutic measures should be initiated. Mild cases of pseudomembranous colitis usually respond to drug discontinuation alone. In moderate to severe cases, consideration should be given to management with fluids and electrolytes, protein supplementation, and treatment with an antibacterial drug clinically effective against Clostridium difficile.

PRECAUTIONS

General

As with other broad-spectrum antibiotics, prolonged treatment may result in the possible emergence and overgrowth of resistant organisms. Careful observation of the patient is essential. If superinfection occurs during therapy, appropriate measures should be taken.

The dose of ceftibuten may require adjustment in patients with varying degrees of renal insufficiency, particularly in patients with creatinine clearance less than 50 mL/min or undergoing hemodialysis (see DOSAGE AND ADMINISTRATION). Ceftibuten is readily dialyzable. Dialysis patients should be monitored carefully, and administration of ceftibuten should occur immediately following dialysis.

Ceftibuten should be prescribed with caution to individuals with a history of gastrointestinal disease, particularly colitis.

Information to Patients

Patients should be informed that:

- If the patient is diabetic, he/she should be informed that CEDAX Oral Suspension contains 1 gram sucrose per teaspoon of suspension.
- CEDAX Oral Suspension should be taken at least 2 hours before a meal or at least 1 hour after a meal (see CLINICAL PHARMACOLOGY, Food Effect on Absorption).

Drug Interactions

Theophylline

Twelve healthy male volunteers were administered one 200-mg ceftibuten capsule twice daily for 6 days. With the morning dose of ceftibuten on day 6, each volunteer received a single intravenous infusion of theophylline (4 mg/kg). The pharmacokinetics of theophylline were not altered. The effect of ceftibuten on the pharmacokinetics of theophylline administered orally has not been investigated.

Antacids or H2-receptor antagonists

The effect of increased gastric pH on the bioavailability of ceftibuten was evaluated in 18 healthy adult volunteers. Each volunteer was administered one 400-mg ceftibuten capsule. A single dose of liquid antacid did not affect the Cmax or AUC of ceftibuten; however, 150 mg of ranitidine q12h for 3 days increased the ceftibuten Cmax by 23% and ceftibuten AUC by 16%. The clinical relevance of these increases is not known.

Drug/Laboratory Test Interactions

There have been no chemical or laboratory test interactions with ceftibuten noted to date. False-positive direct Coombs' tests have been reported during treatment with other cephalosporins. Therefore, it should be recognized that a positive Coombs' test could be due to the drug. The results of assays using red cells from healthy subjects to determine whether ceftibuten would cause direct Coombs' reactions in vitro showed no positive reaction at ceftibuten concentrations as high as 40 µg/mL.

Carcinogenesis, Mutagenesis, Impairment of Fertility

Long-term animal studies have not been performed to evaluate the carcinogenic potential of ceftibuten. No mutagenic effects were seen in the following studies: in vitro chromosome assay in human lymphocytes, in vivo chromosome assay in mouse bone marrow cells, Chinese Hamster Ovary (CHO) cell point mutation assay at the hypoxanthine-guanine phosphoribosyl transferase (HGPRT) locus, and in a bacterial reversion point mutation test (Ames). No impairment of fertility occurred when rats were administered ceftibuten orally up to 2000 mg/kg/day (approximately 43 times the human dose based on mg/m^2/day).

Pregnancy

Teratogenic effects

Pregnancy Category B

Ceftibuten was not teratogenic in the pregnant rat at oral doses up to 400 mg/kg/day (approximately 8.6 times the human dose based on mg/m^2/day). Ceftibuten was not teratogenic in the pregnant rabbit at oral doses up to 40 mg/kg/day (approximately 1.5 times the human dose based on mg/m^2/day) and has revealed no evidence of harm to the fetus. There are no adequate and well-controlled studies in pregnant women. Because animal reproduction studies are not always predictive of human response, this drug should be used during pregnancy only if clearly needed.

Labor and Delivery

Ceftibuten has not been studied for use during labor and delivery. Its use during such clinical situations should be weighed in terms of potential risk and benefit to both mother and fetus.

Nursing Mothers

It is not known whether ceftibuten (at recommended dosages) is excreted in human milk. Because many drugs are excreted in human milk, caution should be exercised when ceftibuten is administered to a nursing woman.

Pediatric Use

The safety and efficacy of ceftibuten in infants less than 6 months of age has not been established.

Geriatric Patients

The usual adult dosage recommendation may be followed for patients in this age group. However, these patients should be monitored closely, particularly their renal function, as dosage adjustment may be required.

ADVERSE EVENTS

Clinical Trials

CEDAX CAPSULES (adult patients)

In clinical trials, 1728 adult patients (1092 US and 636 international) were treated with the recommended dose of ceftibuten capsules (400 mg per day). There were no deaths or permanent disabilities thought due to drug toxicity in any of the patients in these studies. Thirty-six of 1728 (2%) patients discontinued medication due to adverse events thought by the investigators to be possibly, probably, or almost certainly related to drug toxicity. The discontinuations were primarily for gastrointestinal disturbances, usually diarrhea, vomiting, or nausea. Six of 1728 (0.3%) patients were discontinued due to rash or pruritus thought related to ceftibuten administration.

In the US trials, the following adverse events were thought by the investigators to be possibly, probably, or almost certainly related to ceftibuten capsules in multiple-dose clinical trials (n = 1092 ceftibuten-treated patients).

ADVERSE REACTIONS
CEFTIBUTEN CAPSULES
US CLINICAL TRIALS IN ADULT PATIENTS (n = 1092)

Incidence equal to or greater than 1%

Nausea

4%

Headache

3%

Diarrhea

3%

Dyspepsia

2%

Dizziness

1%

Abdominal pain

1%

Vomiting

1%

Incidence less than 1% but greater than 0.1%

Anorexia

Constipation

Dry mouth

Dyspnea

Dysuria

Eructation

Fatigue

Flatulence

Loose stools

Moniliasis

Nasal congestion

Paresthesia

Pruritus

Rash

Somnolence

Taste perversion

Urticaria

Vaginitis

LABORATORY VALUE CHANGES [Changes in laboratory values with possible clinical significance regardless of whether or not the investigator thought that the change was due to drug toxicity.]
CEFTIBUTEN CAPSULES
US CLINICAL TRIALS IN ADULT PATIENTS
Incidence equal to or greater than 1% | ↑ BUN | 4%
Incidence equal to or greater than 1% | ↑ Eosinophils | 3%
 | ↓ Hemoglobin | 2%
 | ↑ ALT (SGPT) | 1%
 | ↑ Bilirubin | 1%
Incidence less than 1% but greater than 0.1% | ↑ Alk phosphatase
Incidence less than 1% but greater than 0.1% | ↑ Creatinine
 | ↑ Platelets
 | ↓ Platelets
 | ↓ Leukocytes
 | ↑ AST (SGOT)

CEDAX ORAL SUSPENSION (pediatric patients)

In clinical trials, 1152 pediatric patients (772 US and 380 international), 97% of whom were younger than 12 years of age, were treated with the recommended dose of ceftibuten (9 mg/kg once daily up to a maximum dose of 400 mg per day) for 10 days. There were no deaths, life-threatening adverse events, or permanent disabilities in any of the patients in these studies. Eight of 1152 (<1%) patients discontinued medication due to adverse events thought by the investigators to be possibly, probably, or almost certainly related to drug toxicity. The discontinuations were primarily (7 out of 8) for gastrointestinal disturbances, usually diarrhea or vomiting. One patient was discontinued due to a cutaneous rash thought possibly related to ceftibuten administration.

In the US trials, the following adverse events were thought by the investigators to be possibly, probably, or almost certainly related to ceftibuten oral suspension in multiple-dose clinical trials (n = 772 ceftibuten-treated patients).

ADVERSE REACTIONS
CEFTIBUTEN ORAL SUSPENSION
US CLINICAL TRIALS IN PEDIATRIC PATIENTS (n = 772)
Incidence equal to or greater than 1% | Diarrhea [NOTE: The incidence of diarrhea in pediatric patients ≤2 years old was 8% (23/301) compared with 2% (9/471) in pediatric patients >2 years old.] | 4%
Incidence equal to or greater than 1% | Vomiting | 2%
 | Abdominal pain | 2%
 | Loose stools | 2%
Incidence less than 1% but greater than 0.1% | Agitation
Incidence less than 1% but greater than 0.1% | Anorexia
 | Dehydration
 | Diaper dermatitis
 | Dizziness
 | Dyspepsia
 | Fever
 | Headache
 | Hematuria
 | Hyperkinesia
 | Insomnia
 | Irritability
 | Nausea
 | Pruritus
 | Rash
 | Rigors
 | Urticaria

LABORATORY VALUE CHANGES [Changes in laboratory values with possible clinical significance regardless of whether or not the investigator thought that the change was due to drug toxicity.]
CEFTIBUTEN ORAL SUSPENSION
US CLINICAL TRIALS IN ADULT PATIENTS
Incidence equal to or greater than 1% | ↑ Eosinophils | 3%
Incidence equal to or greater than 1% | ↑ BUN | 2%
Incidence equal to or greater than 1% | ↓ Hemoglobin | 1%
 | ↑ Platelets | 1%
Incidence less than 1% but greater than 0.1% | ↑ ALT (SGPT)
Incidence less than 1% but greater than 0.1% | ↑ AST (SGOT)
Incidence less than 1% but greater than 0.1% | ↑ Alk phosphatase
 | ↑ Platelets
 | ↑ Bilirubin
 | ↑ Creatinine

In Post-marketing Experience

The following adverse experiences have been reported during worldwide post-marketing surveillance: aphasia, jaundice, melena, psychosis, serum sickness-like reactions, stridor, Stevens-Johnson syndrome, and toxic epidermal necrolysis.

Cephalosporin-class Adverse Reactions

In addition to the adverse reactions listed above that have been observed in patients treated with ceftibuten capsules, the following adverse events and altered laboratory tests have been reported for cephalosporin-class antibiotics:

allergic reactions, anaphylaxis, drug fever, Stevens-Johnson syndrome, renal dysfunction, toxic nephropathy, hepatic cholestasis, aplastic anemia, hemolytic anemia, hemorrhage, false-positive test for urinary glucose, neutropenia, pancytopenia, and agranulocytosis. Pseudomembranous colitis; onset of symptoms may occur during or after antibiotic treatment (see WARNINGS).

Several cephalosporins have been implicated in triggering seizures, particularly in patients with renal impairment when the dosage was not reduced (see DOSAGE AND ADMINISTRATION and OVERDOSAGE). If seizures associated with drug therapy occur, the drug should be discontinued. Anticonvulsant therapy can be given if clinically indicated.

OVERDOSAGE

Overdosage of cephalosporins can cause cerebral irritation leading to convulsions. Ceftibuten is readily dialyzable and significant quantities (65% of plasma concentrations) can be removed from the circulation by a single hemodialysis session. Information does not exist with regard to removal of ceftibuten by peritoneal dialysis.

DOSAGE AND ADMINISTRATION

The recommended doses of CEDAX Oral Suspension are presented in the table below. CEDAX Oral Suspension must be administered at least 2 hours before or 1 hour after a meal.

Type of infection (as qualified in the INDICATIONS AND USAGE section of this labeling)

Daily Maximum Dose

Dose and Frequency

Duration

ADULTS (12 years of age and older):

400 mg

400 mg QD

10 days

Acute Bacterial Exacerbations of Chronic Bronchitis due to H. influenzae (including β-lactamase-producing strains), M. catarrhalis (including β-lactamase-producing strains), or Streptococcus pneumoniae (penicillin-susceptible strains only). (See INDICATIONS AND USAGE - NOTE.)

Pharyngitis and tonsillitis due to S. pyogenes. Acute Bacterial Otitis Media due to H. influenzae (including β-lactamase-producing strains), M. catarrhalis (including β-lactamase-producing strains), or S. pyogenes. (See INDICATIONS AND USAGE - NOTE.)

PEDIATRIC PATIENTS:

400 mg

9 mg/kg QD

10 days

Pharyngitis and tonsillitis due to S. pyogenes. Acute Bacterial Otitis Media due to H. influenzae (including β-lactamase-producing strains), and M. catarrhalis (including β-lactamase-producing strains), or S. pyogenes. (See INDICATIONS AND USAGE - NOTE.)

CEFTIBUTEN ORAL SUSPENSION
PEDIATRIC DOSAGE CHART
CHILD'S WEIGHT | 90 mg/5 mL
10 kg 22 lbs | 1 tsp QD
20 kg 44 lbs | 2 tsp QD
40 kg 88 lbs | 4 tsp QD

Pediatric patients weighing more than 45 kg should receive the maximum daily dose of 400 mg.

Renal Impairment

CEDAX Capsules and CEDAX Oral Suspension may be administered at normal doses in the presence of impaired renal function with creatinine clearance of 50 mL/min or greater. The recommendations for dosing in patients with varying degrees of renal insufficiency are presented in the following table.

Creatinine Clearance (mL/min) | Recommended Dosing Schedules
>50 | 9 mg/kg or 400 mg Q24h (normal dosing schedule)
30-49 | 4.5 mg/kg or 200 mg Q24h
5-29 | 2.25 mg/kg or 100 mg Q24h

Hemodialysis Patients

In patients undergoing hemodialysis two or three times weekly, a single 400-mg dose of ceftibuten capsules or a single dose of 9 mg/kg (maximum of 400 mg of ceftibuten) oral suspension may be administered at the end of each hemodialysis session.

Directions for Mixing CEDAX Oral Suspension

Final Concentration | Bottle Size | Amount of Water | Directions
 | 60 mL | Suspend in 53 mL of water | First tap the bottle to loosen powder. Then add water in two portions, shaking well after each aliquot.
90 mg per 5 mL | 90 mL | Suspend in 78 mL of water | First tap the bottle to loosen powder. Then add water in two portions, shaking well after each aliquot.
 | 120 mL | Suspend in 103 mL of water | First tap the bottle to loosen powder. Then add water in two portions, shaking well after each aliquot.

After mixing, the suspension may be kept for 14 days and must be stored in the refrigerator. Keep tightly closed. Shake well before each use. Discard any unused portion after 14 days.

HOW SUPPLIED

CEDAX Capsules, containing 400 mg of ceftibuten (as ceftibuten dihydrate) are white, opaque capsules imprinted with the product name and strength, are available as follows:

20 Capsules/Bottle (NDC 59630-820-20)

STORAGE AND HANDLING

Store the capsules between 2° and 25°C (36° and 77°F). Replace cap securely after each opening.

CEDAX Oral Suspension is an off-white to cream-colored powder that, when reconstituted as directed, contains ceftibuten equivalent to 90 mg/5 mL, supplied as follows:

90 mg/5 mL

18 mg/mL | 60-mL Bottle | (NDC 59630-821-60)
18 mg/mL | 90-mL Bottle | (NDC 59630-821-90)
18 mg/mL | 120-mL Bottle | (NDC 59630-821-12)

Prior to reconstitution, the powder must be stored between 2° and 25°C (36° and 77°F). Once it is reconstituted, the oral suspension is stable for 14 days when stored in the refrigerator between 2° and 8°C (36° and 46°F).

CLINICAL STUDIES

Acute Bacterial Exacerbations of Chronic Bronchitis

Three clinical trials (two domestic, the third abroad) have been conducted testing ceftibuten in the treatment of acute exacerbations of chronic bronchitis (AECB). Overall, the clinical outcome among patients who had signs and symptoms of AECB, who had a gram stain showing a predominance of PMNs and few epithelial cells, and who were evaluated at approximately 1 to 2 weeks after completing therapy were equivalent to comparators. The bacterial eradication rates of specific pathogens are presented below.

BACTERIOLOGICAL OUTCOME
ACUTE BACTERIAL EXACERBATIONS OF CHRONIC BRONCHITIS
 |  | Ceftibuten 400 mg QD | Control
Bacteriological Eradication Rates
 | Haemophilus influenzae | 45/62 (73%) | 26/36 (72%)
 | H. parainfluenzae | 10/10 | 4/6
 | Moraxella catarrhalis | 33/46 (72%) | 32/34 (94%)
 | Streptococcus pneumoniae | 23/35 (66%) | 14/20 (70%)

Acute Bacterial Otitis Media

Four clinical trials (three domestic, the fourth abroad) have been conducted testing ceftibuten in the treatment of acute bacterial otitis media. Overall, the clinical outcome among patients who had signs and symptoms of acute bacterial otitis media and who were evaluated at approximately 1 to 2 weeks after completing therapy were equivalent to comparators. Tympanocentesis was performed on patients in three of the above-mentioned studies; the bacterial eradication rates of specific pathogens are presented below.

BACTERIOLOGICAL OUTCOME
ACUTE BACTERIAL OTITIS MEDIA
 |  | Ceftibuten 9 mg/kg QD | Control
Bacteriological Eradication Rates
 | Haemophilus influenzae | 56/67 (81%) | 29/38 (76%)
 | Moraxella catarrhalis | 20/26 (77%) | 13/17 (77%)
 | Streptococcus pneumoniae | 68/105 (65%) | 35/40 (88%)
 | Streptococcus pyogenes | 13/15 (87%) | 5/5

REFERENCES

1. National Committee for Clinical Laboratory Standards. Methods for Dilution Antimicrobial Susceptibility Tests for Bacteria that Grow Aerobically – Third Edition. Approved Standard NCCLS Document M7-A3, Vol. 13, No. 25, NCCLS, Villanova, PA. December, 1993.
2. National Committee for Clinical Laboratory Standards. Performance Standards for Antimicrobial Disk Susceptibility Tests – Fifth Edition. Approved Standard NCCLS Document M2-A5, Vol. 13, No. 24, NCCLS, Villanova, PA. December, 1993.

Sciele™
Pharma, Inc.
A SHIONOGI COMPANY

For inquires call 1-800-849-9707 ext. 1454

Sciele Pharma, Inc., Atlanta, GA 30328
Manufactured by Schering Corporation CED01PIB02
Distributed by Sciele Pharma, Inc.

Rev. 06/09

B-33605501
25014456T

PRINCIPAL DISPLAY PANEL - 400 mg Capsule Label

NDC 59630-820-20

CEDAX®
(ceftibuten
capsules)

400 mg

For Oral Administration

Rx only

20 Capsules

Sciele™
Pharma, Inc.
A SHIONOGI COMPANY

PRINCIPAL DISPLAY PANEL - 60 mL Carton

NDC 59630-821-60

CEDAX®
(ceftibuten for
oral suspension)

90
mg per 5 mL

60 mL (when reconstituted)

Rx only

Sciele™
Pharma, Inc.
A SHIONOGI COMPANY

PRINCIPAL DISPLAY PANEL - 90 mL Carton

NDC 59630-821-90

CEDAX®
(ceftibuten for
oral suspension)

90
mg per 5 mL

90 mL (when reconstituted)

Rx only

Sciele™
Pharma, Inc.
A SHIONOGI COMPANY

PRINCIPAL DISPLAY PANEL - 120 mL Carton

NDC 59630-821-12

CEDAX®
(ceftibuten for
oral suspension)

90
mg per 5 mL

120 mL (when reconstituted)

Rx only

Sciele™
Pharma, Inc.
A SHIONOGI COMPANY